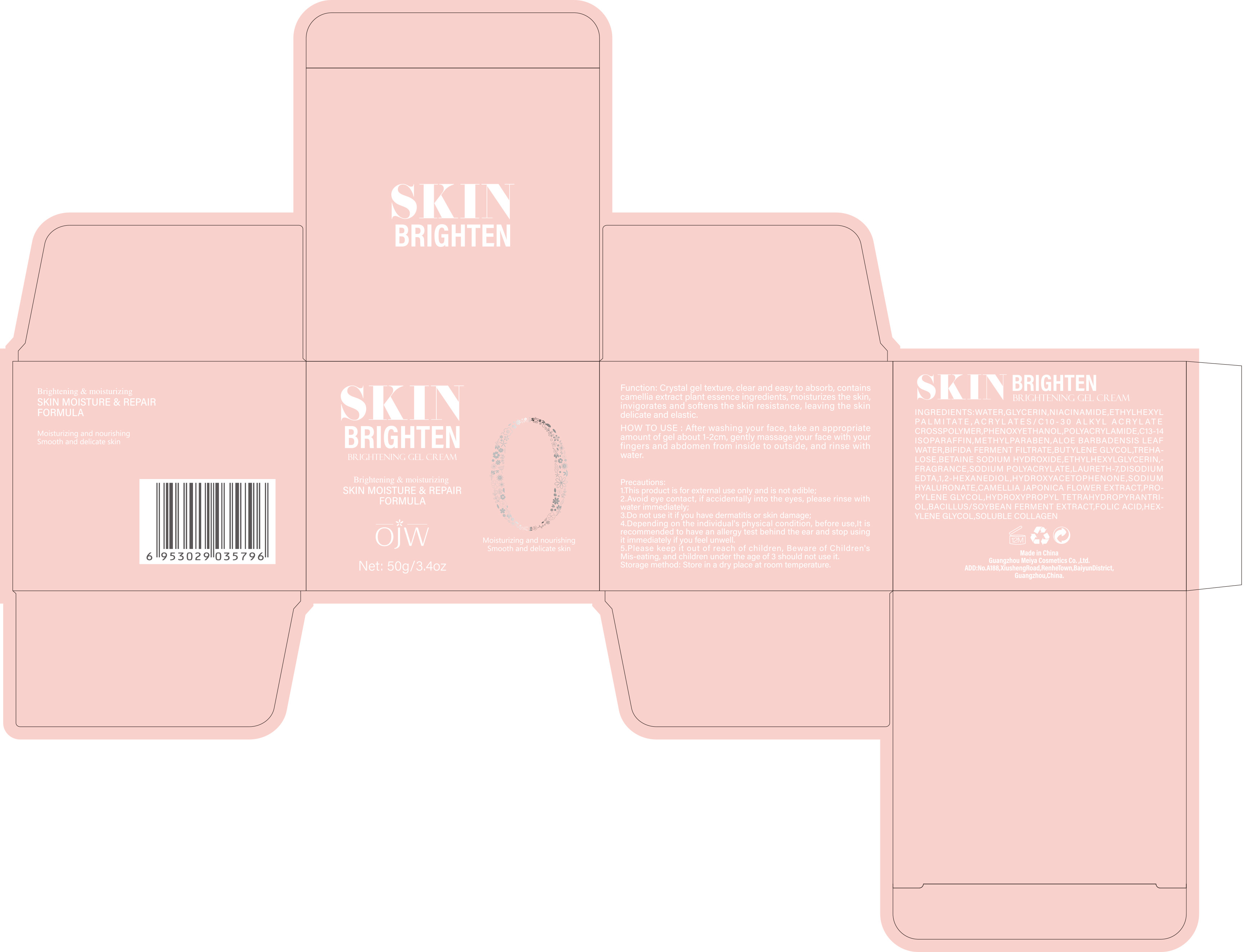 DRUG LABEL: Brightening Gel Cream
NDC: 84673-004 | Form: EMULSION
Manufacturer: Guangzhou Meiya Cosmetics Co.,Ltd.
Category: otc | Type: HUMAN OTC DRUG LABEL
Date: 20240917

ACTIVE INGREDIENTS: NIACINAMIDE 2 g/1 mg
INACTIVE INGREDIENTS: SODIUM HYDROXIDE 1 g/1 mg; BUTYLENE GLYCOL 1.1 g/1 mg; TREHALOSE 1.1 g/1 mg; LAURETH-7 0.035 g/1 mg; BETAINE 1.1 g/1 mg; FOLIC ACID 1 g/1 mg; HEXYLENE GLYCOL 1 g/1 mg; 1,2-HEXANEDIOL 0.00048 g/1 mg; METHYLPARABEN 0.15 g/1 mg; PHENOXYETHANOL 0.45 g/1 mg; ETHYLHEXYLGLYCERIN 1 g/1 mg; GLYCERIN 5 g/1 mg; HYDROXYPROPYL TETRAHYDROPYRANTRIOL 1 g/1 mg; C13-14 ISOPARAFFIN 0.175 g/1 mg; WATER 88.5 g/1 mg; ETHYLHEXYL PALMITATE 1 g/1 mg

ACTIVE INGREDIENT

IACINAMIDE 2%

PURPOSE

Function: Crystal gel texture, clear and easy to absorb, contains camellia extract plant essence ingredients, moisturizes the skin, invigorates and softens the skin resistance, leaving the skin delicate and elastic.

INDICATIONS AND USAGE

HOW TO USE : After washing your face, take an appropriate amount of gel about 1-2cm, gently massage your face with your fingers and abdomen from inside to outside, and rinse with water.

WARNINGS

1. This product is for external use only and is not edible;

2. Avoid eye contact, if accidentally into the eyes, please rinse with water immediately;

3. Do not use it if you have dermatitis or skin damage;

4. Depending on the individual's physical condition, before use,It is recommended to have an allergy test behind the ear and stop using it immediately if you feel unwell.

5. Please keep it out of reach of children, Beware of Children's Mis-eating, and children under the age of 3 should not use it.

STOP USE

1. Avoid eye contact, if accidentally into the eyes, please rinse with water immediately;

2. Do not use it if you have dermatitis or skin damage;

3. Depending on the individual's physical condition, before use,It is recommended to have an allergy test behind the ear and stop using it immediately if you feel unwell.

DO NOT USE

1.This product is for external use only and is not edible;

2.Depending on the individual's physical condition, before use,It is recommended to have an allergy test behind the ear and stop using it immediately if you feel unwell.

3. Please keep it out of reach of children, Beware of Children's Mis-eating, and children under the age of 3 should not use it.

WHEN USING

1. This product is for external use only and is not edible;

2. Avoid eye contact, if accidentally into the eyes, please rinse with water immediately;

3. Do not use it if you have dermatitis or skin damage;

4. Depending on the individual's physical condition, before use,It is recommended to have an allergy test behind the ear and stop using it immediately if you feel unwell.

5. Please keep it out of reach of children, Beware of Children's Mis-eating, and children under the age of 3 should not use it.

KEEP OUT OF REACH OF CHILDREN

Please keep it out of reach of children, Beware of Children's Mis-eating, and children under the age of 3 should not use it.

DOSAGE AND ADMINISTRATION

After washing your face, take an appropriate amount of gel about 1-2cm, gently massage your face with your fingers and abdomen from inside to outside, and rinse with water.